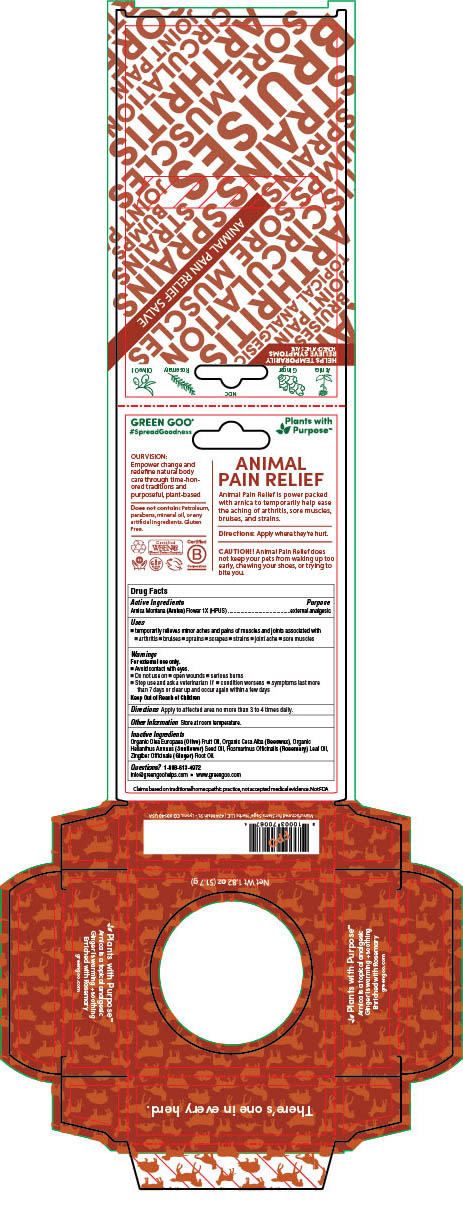 DRUG LABEL: Animal Pain Relief
NDC: 70994-304 | Form: SALVE
Manufacturer: Spry Life LLC
Category: homeopathic | Type: HUMAN OTC DRUG LABEL
Date: 20251215

ACTIVE INGREDIENTS: ARNICA MONTANA FLOWER 1 [hp_X]/17 g
INACTIVE INGREDIENTS: OLIVE OIL; YELLOW WAX; SUNFLOWER OIL; ROSEMARY OIL; GINGER OIL

Animal Pain Relief

Purpose

External Analgesic

OTC Active Ingredients

Arnica Montana (Arnica) Flower 1X (HPUS)

Indications & Usage

■ temporarily reief of minor aches and pains of muscles and joints associated with ■ arthritis ■ bruises ■ sprains ■ scrapes ■ strains ■ joint ache ■ sore muscles

Warnings

For external use only.

■ Avoid contact with eyes.
■ Do not use on ■ on open wounds ■ animal bites ■ serious burns
■ Stop use and ask a doctor if ■ condition worsens ■ symptoms last more than 7 days or clear up and occur again within a few days

Keep Out of Reach of Children

Storage and Handling

Store at room temperature.

Dosage & Administration

Apply to affected area no more than 3 to 4 times daily.

Inactive Ingredients

Organic Olea Europaea (Olive) Fruit Oil, Organic Cera Alba (Beeswax), Organic Helianthus Annuus (Sunflower) Seed Oil, Rosmarinus Officinalis (Rosemary) Leaf Oil, Zingiber Officinale (Ginger) Root Oil.